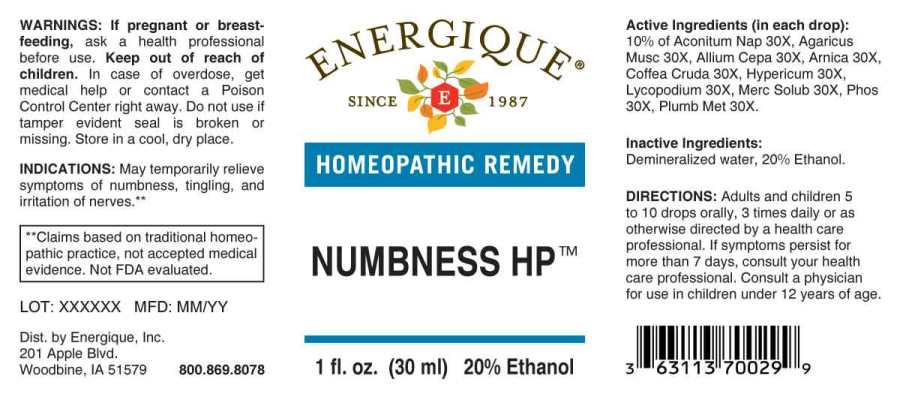 DRUG LABEL: Numbness HP
NDC: 44911-0625 | Form: LIQUID
Manufacturer: Energique, Inc.
Category: homeopathic | Type: HUMAN OTC DRUG LABEL
Date: 20241029

ACTIVE INGREDIENTS: ACONITUM NAPELLUS WHOLE 30 [hp_X]/1 mL; AMANITA MUSCARIA FRUITING BODY 30 [hp_X]/1 mL; ONION 30 [hp_X]/1 mL; ARNICA MONTANA WHOLE 30 [hp_X]/1 mL; ARABICA COFFEE BEAN 30 [hp_X]/1 mL; HYPERICUM PERFORATUM WHOLE 30 [hp_X]/1 mL; LYCOPODIUM CLAVATUM SPORE 30 [hp_X]/1 mL; MERCURIUS SOLUBILIS 30 [hp_X]/1 mL; PHOSPHORUS 30 [hp_X]/1 mL; LEAD 30 [hp_X]/1 mL
INACTIVE INGREDIENTS: WATER; ALCOHOL

DRUG FACTS:

ACTIVE INGREDIENTS:

(in each drop): 10% of Aconitum Napellus 30X, Agaricus Muscarius 30X, Allium Cepa 30X, Arnica Montana 30X, Coffea Cruda 30X, Hypericum Perforatum 30X, Lycopodium Clavatum 30X, Mercurius Solubilis 30X, Phosphorus 30X, Plumbum Metallicum 30X.

INDICATIONS:

May temporarily relieve symptoms of numbness, tingling, and irritation of nerves.**

**Claims based on traditional homeopathic practice, not accepted medical evidence. Not FDA evaluated.

WARNING:

If pregnant or breast-feeding, ask a health professional before use.
Keep out of reach of children. In case of overdose, get medical help or contact a Poison Control Center right away.
Do not use if tamper evident seal is broken or missing. Store in a cool, dry place.

Keep out of reach of children. In case of overdose, get medical help or contact a Poison Control Center right away.

DIRECTIONS:

Adults and children 5 to 10 drops orally, 3 times daily or as otherwise directed by a health care professional. If symptoms persist for more than 7 days, consult your health care professional. Consult a physician for use in children under 12 years of age.

INDICATIONS:

May temporarily relieve symptoms of numbness, tingling, and irritation of nerves.**

**Claims based on traditional homeopathic practice, not accepted medical evidence. Not FDA evaluated.

INACTIVE INGREDIENTS:

Demineralized water, 20% Ethanol

QUESTIONS:

Dist. by Energique, Inc.
201 Apple Blvd
Woodbine, IA 51579 800-869-8078

PACKAGE LABEL DISPLAY:

ENERGIQUE

SINCE 1987

HOMEOPATHIC REMEDY

NUMBNESS HP

1 fl. oz. (30 ml)